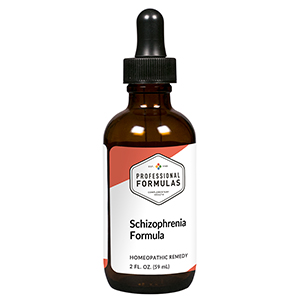 DRUG LABEL: Schizophrenia Formula
NDC: 63083-2113 | Form: LIQUID
Manufacturer: Professional Complementary Health Formulas
Category: homeopathic | Type: HUMAN OTC DRUG LABEL
Date: 20190815

ACTIVE INGREDIENTS: HORSE CHESTNUT 3 [hp_X]/59 mL; HELIANTHUS ANNUUS FLOWERING TOP 3 [hp_X]/59 mL; PASSIFLORA INCARNATA FLOWER 4 [hp_X]/59 mL; SEPIA ESCULENTA BONE 30 [hp_X]/59 mL
INACTIVE INGREDIENTS: ALCOHOL; WATER

C113

ACTIVE INGREDIENTS

So-Lo-Tzu 3X
Hsiang-Jih-Kuei-Hua-Pan 3X, 6X
Ji-Qing-Hua 4X
Wu-Tsei-Ku 30X

QUESTIONS

Professional Formulas

PO Box 2034 Lake Oswego, OR 97035

INDICATIONS

For the temporary relief of confusion, memory loss, disorientation, anxiousness, feelings of anger or fear, or mood swings.*

PURPOSE

*Claims based on traditional homeopathic practice, not accepted medical evidence. Not FDA evaluated.

WARNINGS

Persistent symptoms may be a sign of a serious condition. Consult a doctor immediately if symptoms persist or are accompanied by hallucinations or thoughts of harming self or others. Keep out of the reach of children. In case of overdose, get medical help or contact a poison control center right away. If pregnant or breastfeeding, ask a healthcare professional before use.

Keep out of the reach of children.

PREGNANCY OR BREAST FEEDING

If pregnant or breastfeeding, ask a healthcare professional before use.

DIRECTIONS

Place drops under tongue 30 minutes before/after meals. Adults and children 12 years and over: Take 10 drops up to 3 times per day. Consult a physician for use in children under 12 years of age.

OTHER INFORMATION

Tamper resistant. If seal is broken, do not use. After opening, close container tightly and store at room temperature away from heat.

INACTIVE INGREDIENTS

20% ethanol, purified water.

LABEL

Est 1985

Professional Formulas

Complementary Health

Schizophrenia Formula

Homeopathic Remedy

2 FL. OZ. (59 mL)